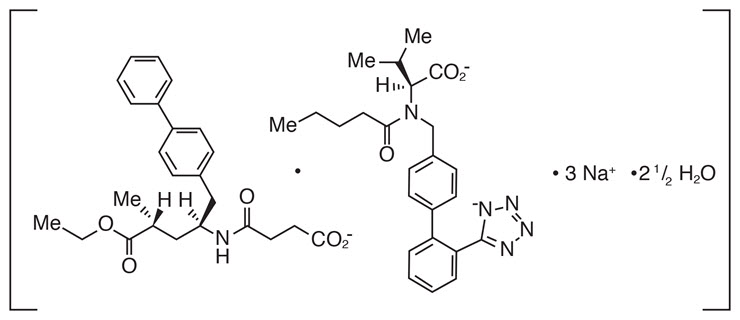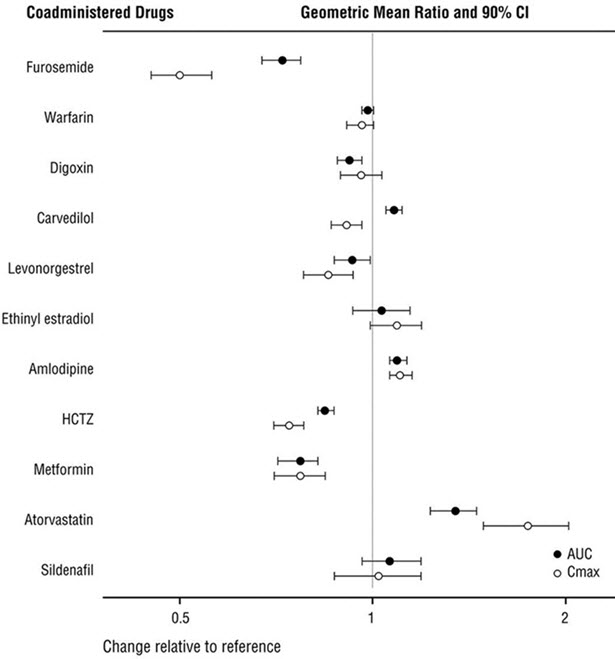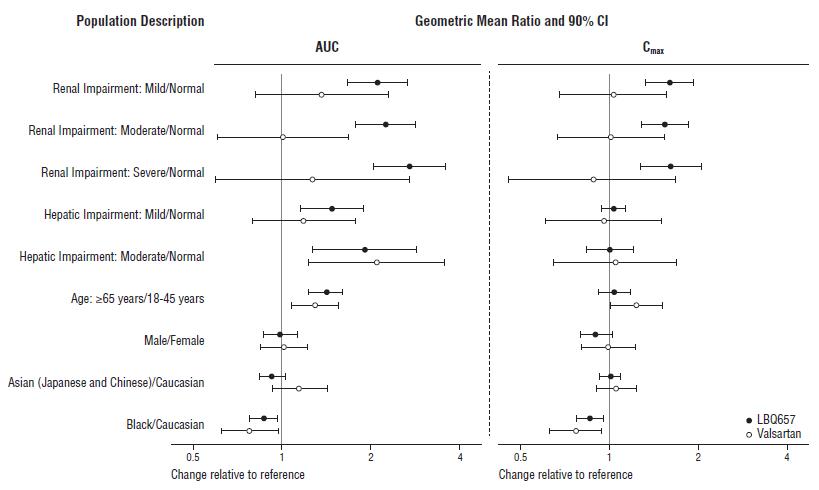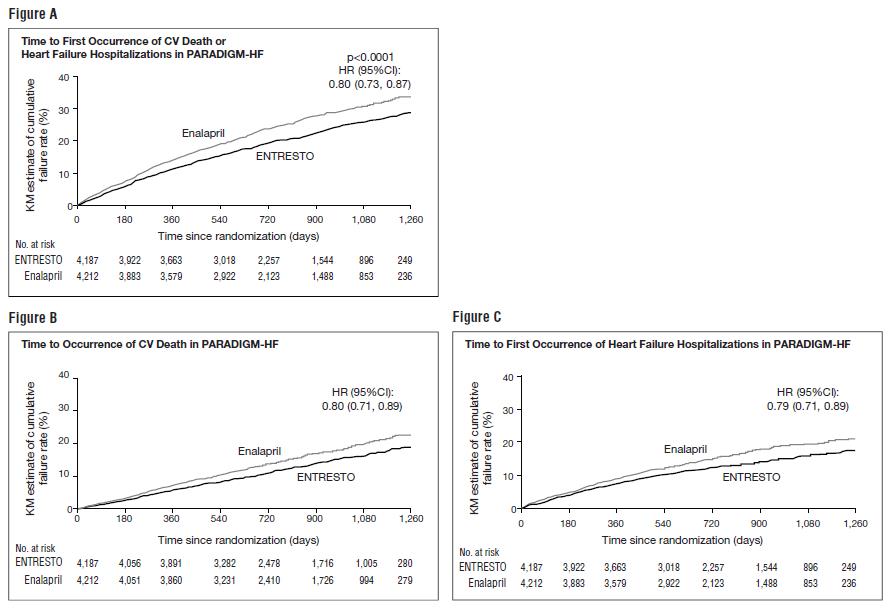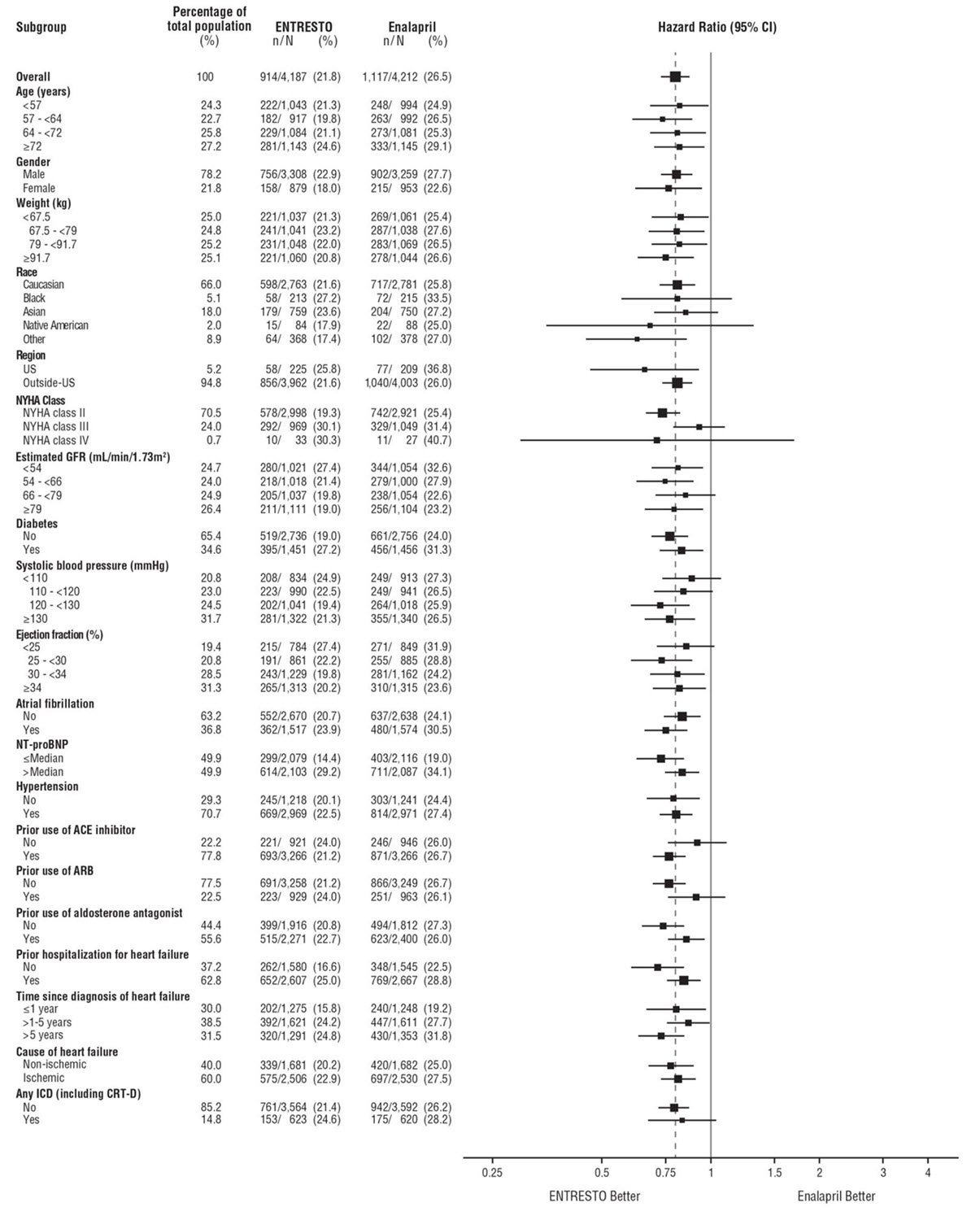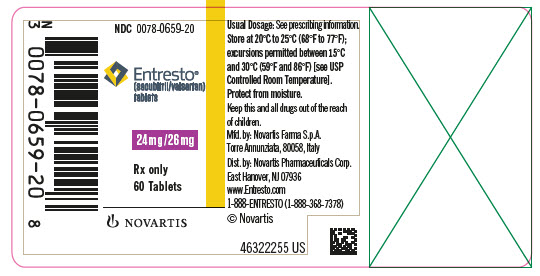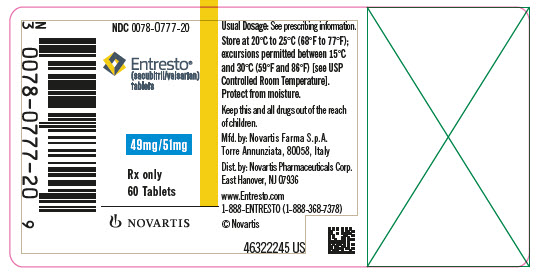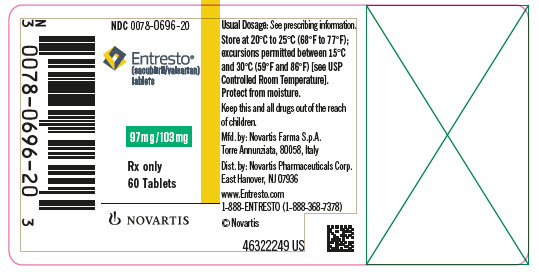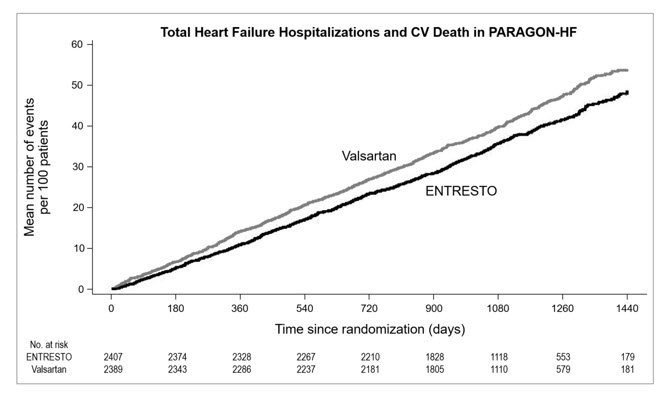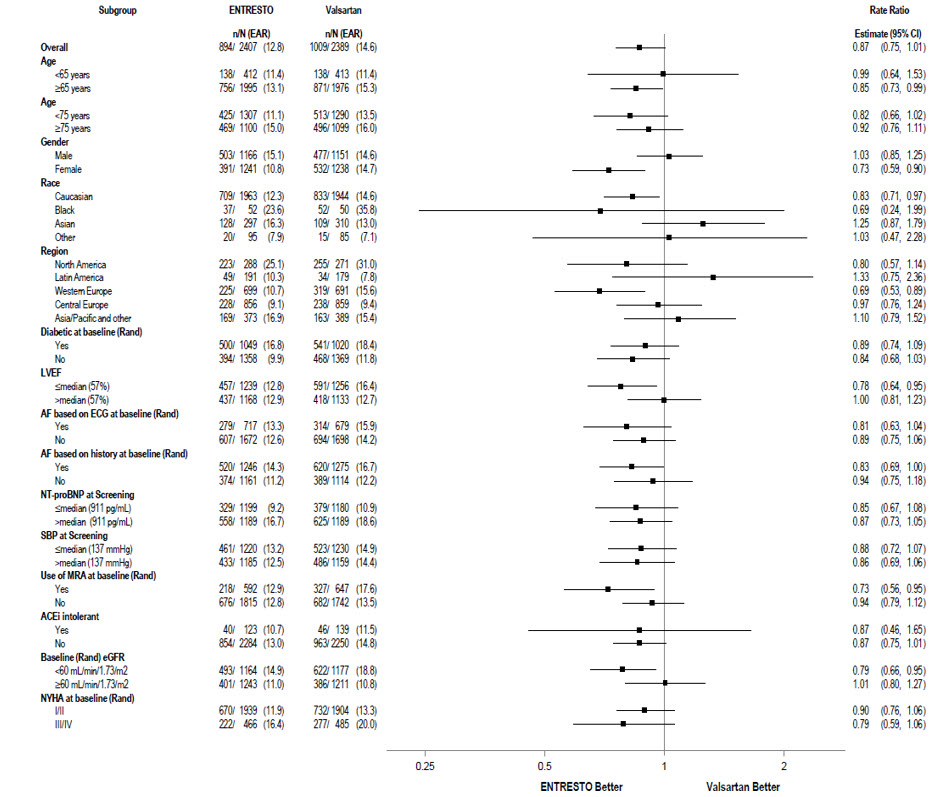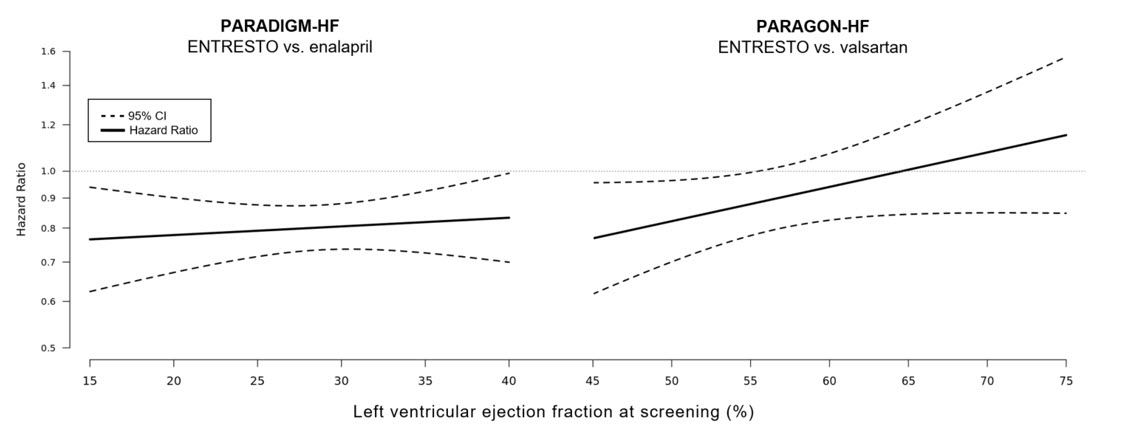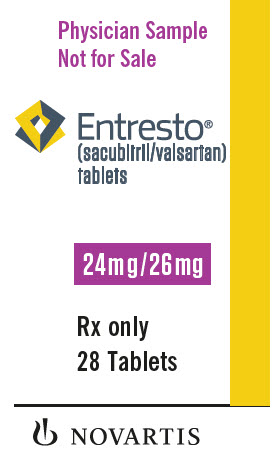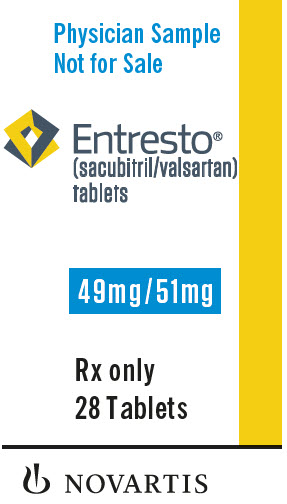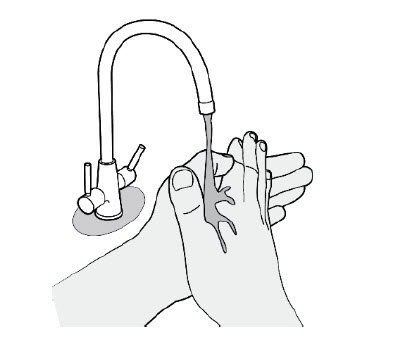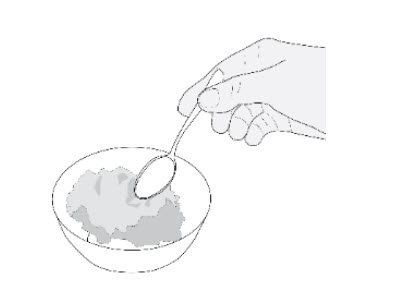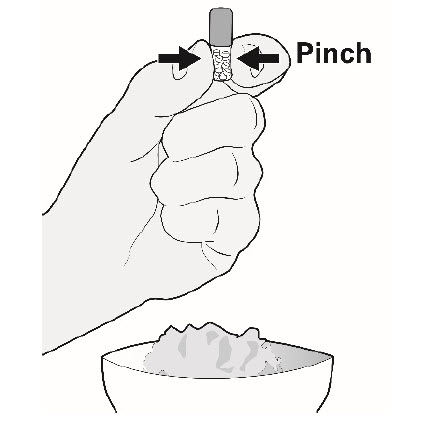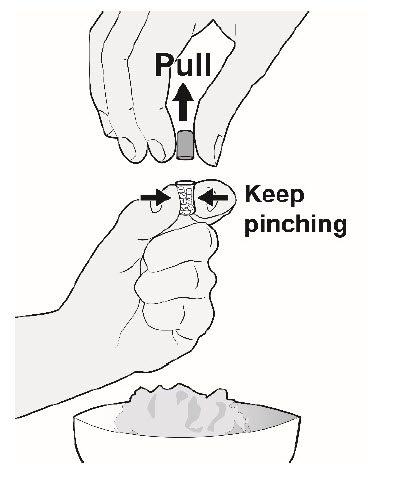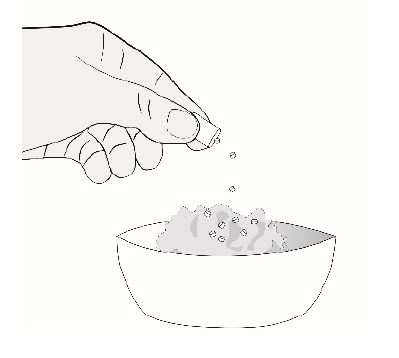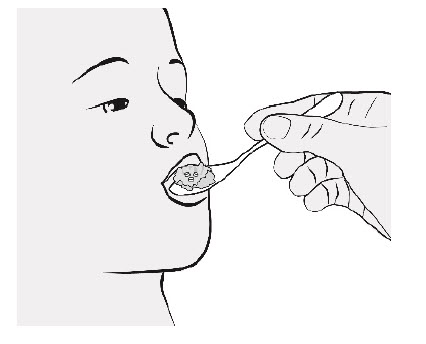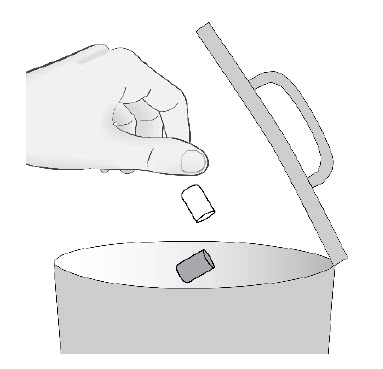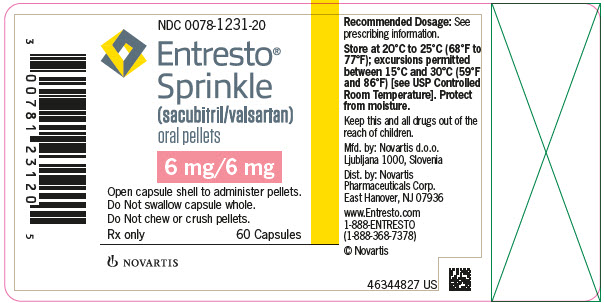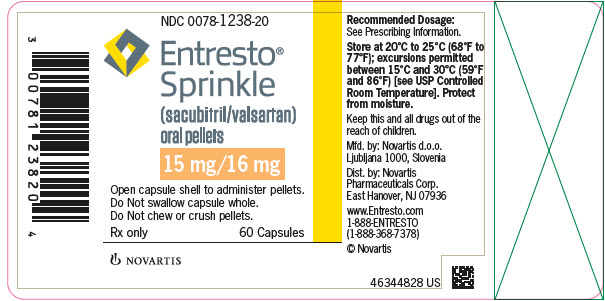 DRUG LABEL: ENTRESTO
NDC: 0078-0659 | Form: TABLET, FILM COATED
Manufacturer: Novartis Pharmaceuticals Corporation
Category: prescription | Type: HUMAN PRESCRIPTION DRUG LABEL
Date: 20251029

ACTIVE INGREDIENTS: SACUBITRIL 24 mg/1 1; VALSARTAN 26 mg/1 1
INACTIVE INGREDIENTS: CELLULOSE, MICROCRYSTALLINE; CROSPOVIDONE; MAGNESIUM STEARATE; TALC; SILICON DIOXIDE; HYDROXYPROPYL CELLULOSE, LOW SUBSTITUTED; HYPROMELLOSES; TITANIUM DIOXIDE; POLYETHYLENE GLYCOL 4000; FERRIC OXIDE RED; FERROSOFERRIC OXIDE

HIGHLIGHTS OF PRESCRIBING INFORMATION

These highlights do not include all the information needed to use ENTRESTO safely and effectively. See full prescribing information for ENTRESTO.
ENTRESTO® (sacubitril and valsartan) tablets, for oral use
ENTRESTO® SPRINKLE (sacubitril and valsartan) oral pellets
Initial U.S. Approval: 2015

WARNING: FETAL TOXICITY

See full prescribing information for complete boxed warning.

- When pregnancy is detected, discontinue ENTRESTO as soon as possible. (5.1)
- Drugs that act directly on the renin-angiotensin system can cause injury and death to the developing fetus. (5.1)

RECENT MAJOR CHANGES

Dosage and Administration (2.3, 2.5) | 4/2024

1 INDICATIONS AND USAGE

ENTRESTO is a combination of sacubitril, a neprilisin inhibitor, and valsartan, an angiotensin II receptor blocker, and is indicated:

- to reduce the risk of cardiovascular death and hospitalization for heart failure in adult patients with chronic heart failure. Benefits are most clearly evident in patients with left ventricular ejection fraction (LVEF) below normal. (1.1)
- for the treatment of symptomatic heart failure with systemic left ventricular systolic dysfunction in pediatric patients aged one year and older. ENTRESTO reduces NT-proBNP and is expected to improve cardiovascular outcomes. (1.2)

2 DOSAGE AND ADMINISTRATION

- The recommended starting dosage for adults is 49 mg/51 mg orally twice daily. The target maintenance dose is 97 mg/103mg orally twice daily. (2.2)
- Adjust adult doses every 2 to 4 weeks to the target maintenance dose, as tolerated by the patient. (2.2)
- For pediatric patients, see the Full Prescribing Information for recommended dosage, titrations, preparation and administration instructions. (2.3, 2.4, 2.5)
- Reduce starting dose to half the usually recommended starting dosage for:
  - patients not currently taking an angiotensin-converting enzyme (ACE) inhibitor or angiotensin II receptor blocker (ARB) or previously taking a low dose of these agents. (2.6)
  - patients with severe renal impairment. (2.7)
  - patients with moderate hepatic impairment. (2.8)

3 DOSAGE FORMS AND STRENGTHS

- Film-coated tablets: 24/26 mg; 49/51 mg; 97/103 mg (3)
- Film-coated oral pellets within capsules: 6 mg/6 mg; 15 mg/16 mg (3)

4 CONTRAINDICATIONS

- Hypersensitivity to any component. (4)
- History of angioedema related to previous ACEi or ARB therapy. (4)
- Concomitant use with ACE inhibitors. (4, 7.1)
- Concomitant use with aliskiren in patients with diabetes. (4, 7.1)

5 WARNINGS AND PRECAUTIONS

- Observe for signs and symptoms of angioedema and hypotension. (5.2, 5.3)
- Monitor renal function and potassium in susceptible patients. (5.4, 5.5)

6 ADVERSE REACTIONS

Adverse reactions occurring greater than or equal to 5% are hypotension, hyperkalemia, cough, dizziness, and renal failure. (6.1)

To report SUSPECTED ADVERSE REACTIONS, contact Novartis Pharmaceuticals Corporation at 1-888-669-6682 or FDA at 1-800-FDA-1088 or www.fda.gov/medwatch.

7 DRUG INTERACTIONS

- Avoid concomitant use with aliskiren in patients with estimated glomerular filtration rate (eGFR) less than 60. (7.1)
- Potassium-sparing diuretics: May lead to increased serum potassium. (7.2)
- Nonsteroidal Anti-Inflammatory Drugs (NSAIDs): May lead to increased risk of renal impairment. (7.3)
- Lithium: Increased risk of lithium toxicity. (7.4)

8 USE IN SPECIFIC POPULATIONS

- Lactation: Breastfeeding not recommended. (8.2)
- Severe Hepatic Impairment: Use not recommended. (2.8, 8.6)

FULL PRESCRIBING INFORMATION

WARNING: FETAL TOXICITY

- When pregnancy is detected, discontinue ENTRESTO as soon as possible (5.1)
- Drugs that act directly on the renin-angiotensin system can cause injury and death to the developing fetus (5.1)

1 INDICATIONS AND USAGE

1.1 Adult Heart Failure

ENTRESTO is indicated to reduce the risk of cardiovascular death and hospitalization for heart failure in adult patients with chronic heart failure. Benefits are most clearly evident in patients with left ventricular ejection fraction (LVEF) below normal.

LVEF is a variable measure, so use clinical judgment in deciding whom to treat [see Clinical Studies (14.1)].

1.2 Pediatric Heart Failure

ENTRESTO is indicated for the treatment of symptomatic heart failure with systemic left ventricular systolic dysfunction in pediatric patients aged one year and older. ENTRESTO reduces NT-proBNP and is expected to improve cardiovascular outcomes.

2 DOSAGE AND ADMINISTRATION

2.1 General Considerations

ENTRESTO is contraindicated with concomitant use of an angiotensin-converting enzyme (ACE) inhibitor. If switching from an ACE inhibitor to ENTRESTO allow a washout period of 36 hours between administration of the two drugs [see Contraindications (4) and Drug Interactions (7.1)].

2.2 Adult Heart Failure

The recommended starting dose of ENTRESTO is 49/51 mg orally twice-daily.

Double the dose of ENTRESTO after 2 to 4 weeks to the target maintenance dose of 97/103 mg twice daily, as tolerated by the patient.

2.3 Pediatric Heart Failure

For the recommended dosage for pediatric patients aged 1 year and older, refer to Table 1 if using the tablets, or Table 2 if using the oral pellets.

Take the recommended dose orally twice daily. Adjust pediatric patient doses every 2 weeks, as tolerated by the patient.

Table 1: Recommended Dose and Titration for Pediatric Patients Using Tablets
 | Titration Step Dose (twice daily)
Weight (kg) | Starting | Second | Final
Less than 40 kg† | 1.6 mg/kg | 2.3 mg/kg | 3.1 mg/kg
At least 40 kg, less than 50 kg | 24 mg/26 mg | 49 mg/51 mg | 72 mg/78 mg‡
At least 50 kg | 49 mg/51 mg | 72 mg/78 mg‡ | 97 mg/103 mg
†Use of the oral suspension or oral pellets (see Table 2) is recommended in these patients. Recommended mg/kg doses are of the combined amount of both sacubitril and valsartan [see Dosage and Administration (2.4, 2.5)].
‡Doses of 72 mg/78 mg can be achieved using three 24 mg/26 mg tablets [see Dosage Forms and Strengths (3)].

Table 2: Recommended Dose and Titration for Pediatric Patients using ENTRESTO SPRINKLE†
 | Titration Step Dose (twice daily)
Weight (kg)* | Starting | Second | Final
Less than 13 (use oral suspension‡) | 1.6 mg/kg | 2.3 mg/kg | 3.1 mg/kg
13 to less than 19 | 12 mg/12 mg (Two 6 mg/6 mg capsules) | 18 mg/18 mg (Three 6 mg/6 mg capsules) | 24 mg/24 mg (Four 6 mg/6 mg capsules)
19 to less than 26 | 18 mg/18 mg (Three 6 mg/6 mg capsules) | 24 mg/24 mg (Four 6 mg/6 mg capsules) | 30 mg/32 mg (Two 15 mg/16 mg capsules)
26 to less than 34 | 24 mg/24 mg (Four 6 mg/6 mg capsules) | 30 mg/32 mg (Two 15 mg/16 mg capsules) | 45 mg/48 mg (Three 15 mg/16 mg capsules)
34 to less than 50* | 30 mg/32 mg (Two 15 mg/16 mg capsules) | 45 mg/48 mg (Three 15 mg/16 mg capsules) | 60 mg/64 mg (Four 15 mg/16 mg capsules)
†When using capsules, more than one capsule may be needed to achieve recommended doses. Oral pellets are contained within each capsule. Use the entire contents of the capsules to achieve the dose.
‡Recommended mg/kg doses are of the combined amount of sacubitril and valsartan [see Dosage and administration (2.4)].
*For patients 50 kg or more, see Table 1.

2.4 Preparation of Oral Suspension Using Tablets

ENTRESTO oral suspension can be substituted at the recommended tablet dosage in patients unable to swallow tablets.

ENTRESTO 800 mg/200 mL oral suspension can be prepared in a concentration of 4 mg/mL (sacubitril/valsartan 1.96/2.04 mg/mL). Use ENTRESTO 49/51 mg tablets in the preparation of the suspension.

To make an 800 mg/200 mL (4 mg/mL) oral suspension, transfer eight tablets of ENTRESTO 49/51 mg film-coated tablets into a mortar. Crush the tablets into a fine powder using a pestle. Add 60 mL of Ora-Plus® into the mortar and triturate gently with pestle for 10 minutes, to form a uniform suspension. Add 140 mL of Ora-Sweet® SF into mortar and triturate with pestle for another 10 minutes, to form a uniform suspension. Transfer the entire contents from the mortar into a clean 200 mL amber colored PET or glass bottle. Place a press-in bottle adapter and close the bottle with a child resistant cap.

The oral suspension can be stored for up to 15 days. Do not store above 25°C (77°F) and do not refrigerate. Shake before each use.

*Ora-Sweet SF® and Ora-Plus® are registered trademarks of Paddock Laboratories, Inc.

2.5 Preparation and Administration of Oral Pellets

ENTRESTO SPRINKLE are oral pellets contained within capsules. Do not swallow the capsules. Do not chew or crush the oral pellets.

ENTRESTO SPRINKLE can also be substituted in patients unable to swallow tablets.

Use the entire contents of the capsules to achieve the dose.

To administer ENTRESTO oral pellets, open the capsule and sprinkle the full content onto 1 to 2 teaspoons of soft food. Consume the food containing the oral pellets immediately after adding them. Empty capsule shells must be discarded after use and not swallowed. Do not administer ENTRESTO oral pellets via nasogastric, gastrostomy, or other enteral tubes because it may cause obstruction of enteral tubes.

2.6 Dose Adjustment for Patients Not Taking an ACE inhibitor or ARB or Previously Taking Low Doses of These Agents

In patients not currently taking an ACE inhibitor or an angiotensin II receptor blocker (ARB) and for patients previously taking low doses of these agents, start ENTRESTO at half the usually recommended starting dose. After initiation, increase the dose every 2 to 4 weeks in adults and every 2 weeks in pediatric patients to follow the recommended dose escalation thereafter [see Dosage and Administration (2.2, 2.3)].

Note: Initiate pediatric patients weighing 40 to 50 kg who meet this criterion at 0.8 mg/kg twice daily using the oral suspension or oral pellets [see Dosage and Administration (2.3, 2.4, 2.5)].

2.7 Dose Adjustment for Severe Renal Impairment

In adults and pediatric patients with severe renal impairment estimated glomerular filtration rate (eGFR less than 30 mL/min/1.73 m^2), start ENTRESTO at half the usually recommended starting dose. After initiation, increase the dose to follow the recommended dose escalation thereafter [see Dosage and Administration (2.2, 2.3)].

Note: Initiate pediatric patients weighing 40 to 50 kg who meet this criterion at 0.8 mg/kg twice daily using the oral suspension or oral pellets [see Dosage and Administration (2.3, 2.4, 2.5)].

No starting dose adjustment is needed for mild or moderate renal impairment.

2.8 Dose Adjustment for Hepatic Impairment

In adults and pediatric patients with moderate hepatic impairment (Child-Pugh B classification), start ENTRESTO at half the usually recommended starting dose. After initiation, increase the dose to follow the recommended dose escalation thereafter [see Dosage and Administration (2.2, 2.3)].

Note: Initiate pediatric patients weighing 40 to 50 kg who meet this criterion at 0.8 mg/kg twice daily using the oral suspension or oral pellets [see Dosage and Administration (2.3, 2.4, 2.5)].

No starting dose adjustment is needed for mild hepatic impairment.

Use in patients with severe hepatic impairment is not recommended.

3 DOSAGE FORMS AND STRENGTHS

ENTRESTO film-coated tablets are supplied as unscored, ovaloid tablets in the following strengths:

- ENTRESTO 24/26 mg, (sacubitril 24 mg and valsartan 26 mg) are violet white and debossed with “NVR” on one side and “LZ” on the other side.
- ENTRESTO 49/51 mg, (sacubitril 49 mg and valsartan 51 mg) are pale yellow and debossed with “NVR” on one side and “L1” on the other side.
- ENTRESTO 97/103 mg, (sacubitril 97 mg and valsartan 103 mg) are light pink and debossed with “NVR” on one side and “L11” on the other side.

ENTRESTO SPRINKLE film-coated oral pellets are contained in a hard capsule in the following strengths:

- ENTRESTO SPRINKLE 6/6 mg, (sacubitril 6 mg and valsartan 6 mg) consists of a white colored cap with “04” and a transparent body with “NVR” and both parts with arrows.
- ENTRESTO SPRINKLE 15/16 mg, (sacubitril 15 mg and valsartan 16 mg) consists of a yellow colored cap with “10” and a transparent body with “NVR” and both parts with arrows.

4 CONTRAINDICATIONS

ENTRESTO is contraindicated:

- in patients with hypersensitivity to any component
- in patients with a history of angioedema related to previous ACE inhibitor or ARB therapy [see Warnings and Precautions (5.2)]
- with concomitant use of ACE inhibitors. Do not administer within 36 hours of switching from or to an ACE inhibitor [see Drug Interactions (7.1)]
- with concomitant use of aliskiren in patients with diabetes [see Drug Interactions (7.1)]

5 WARNINGS AND PRECAUTIONS

5.1 Fetal Toxicity

ENTRESTO can cause fetal harm when administered to a pregnant woman. Use of drugs that act on the renin-angiotensin system during the second and third trimesters of pregnancy reduces fetal renal function and increases fetal and neonatal morbidity and death. When pregnancy is detected, consider alternative drug treatment and discontinue ENTRESTO. However, if there is no appropriate alternative to therapy with drugs affecting the renin-angiotensin system, and if the drug is considered lifesaving for the mother, advise a pregnant woman of the potential risk to the fetus [see Use in Specific Populations (8.1)].

5.2 Angioedema

ENTRESTO may cause angioedema [see Adverse Reactions (6.1)]. If angioedema occurs, discontinue ENTRESTO immediately, provide appropriate therapy, and monitor for airway compromise. ENTRESTO must not be re-administered. In cases of confirmed angioedema where swelling has been confined to the face and lips, the condition has generally resolved without treatment, although antihistamines have been useful in relieving symptoms.

Angioedema associated with laryngeal edema may be fatal. Where there is involvement of the tongue, glottis or larynx, likely to cause airway obstruction, administer appropriate therapy, e.g., subcutaneous epinephrine/adrenaline solution 1:1000 (0.3 mL to 0.5 mL) and take measures necessary to ensure maintenance of a patent airway.

ENTRESTO has been associated with a higher rate of angioedema in Black than in non-Black patients.

Patients with a prior history of angioedema may be at increased risk of angioedema with ENTRESTO [see Adverse Reactions (6.1)]. ENTRESTO must not be used in patients with a known history of angioedema related to previous ACE inhibitor or ARB therapy [see Contraindications (4)]. ENTRESTO should not be used in patients with hereditary angioedema.

5.3 Hypotension

ENTRESTO lowers blood pressure and may cause symptomatic hypotension [see Adverse Reactions (6.1)]. Patients with an activated renin-angiotensin system, such as volume- and/or salt-depleted patients (e.g., those being treated with high doses of diuretics), are at greater risk. Correct volume or salt depletion prior to administration of ENTRESTO or start at a lower dose. If hypotension occurs, consider dose adjustment of diuretics, concomitant antihypertensive drugs, and treatment of other causes of hypotension (e.g., hypovolemia). If hypotension persists despite such measures, reduce the dosage or temporarily discontinue ENTRESTO. Permanent discontinuation of therapy is usually not required.

5.4 Impaired Renal Function

As a consequence of inhibiting the renin-angiotensin-aldosterone system (RAAS), decreases in renal function may be anticipated in susceptible individuals treated with ENTRESTO [see Adverse Reactions (6.1)]. In patients whose renal function depends upon the activity of the renin-angiotensin-aldosterone system (e.g., patients with severe congestive heart failure), treatment with ACE inhibitors and angiotensin receptor antagonists has been associated with oliguria, progressive azotemia and, rarely, acute renal failure and death. Closely monitor serum creatinine, and down-titrate or interrupt ENTRESTO in patients who develop a clinically significant decrease in renal function [see Use in Specific Populations (8.7) and Clinical Pharmacology (12.3)].

As with all drugs that affect the RAAS, ENTRESTO may increase blood urea and serum creatinine levels in patients with bilateral or unilateral renal artery stenosis. In patients with renal artery stenosis, monitor renal function.

5.5 Hyperkalemia

Through its actions on the RAAS, hyperkalemia may occur with ENTRESTO [see Adverse Reactions (6.1)]. Monitor serum potassium periodically and treat appropriately, especially in patients with risk factors for hyperkalemia such as severe renal impairment, diabetes, hypoaldosteronism, or a high potassium diet. Dosage reduction or interruption of ENTRESTO may be required [see Dosage and Administration (2.7)].

6 ADVERSE REACTIONS

Clinically significant adverse reactions that appear in other sections of the labeling include:

- Angioedema [see Warnings and Precautions (5.2)]
- Hypotension [see Warnings and Precautions (5.3)]
- Impaired Renal Function [see Warnings and Precautions (5.4)]
- Hyperkalemia [see Warnings and Precautions (5.5)]

6.1 Clinical Trials Experience

Because clinical trials are conducted under widely varying conditions, adverse reaction rates observed in the clinical trials of a drug cannot be directly compared to rates in the clinical trials of another drug and may not reflect the rates observed in practice.

A total of 6,622 heart failure patients were treated with ENTRESTO in the PARADIGM-HF (vs. enalapril) and PARAGON-HF (vs. valsartan) clinical trials. Of these, 5,085 were exposed for at least 1 year.

Adult Heart Failure

In PARADIGM-HF, patients were required to complete sequential enalapril and ENTRESTO run-in periods of (median) 15 and 29 days, respectively, prior to entering the randomized double-blind period comparing ENTRESTO and enalapril. During the enalapril run-in period, 1,102 patients (10.5%) were permanently discontinued from the study, 5.6% because of an adverse event, most commonly renal dysfunction (1.7%), hyperkalemia (1.7%) and hypotension (1.4%). During the ENTRESTO run-in period, an additional 10.4% of patients permanently discontinued treatment, 5.9% because of an adverse event, most commonly renal dysfunction (1.8%), hypotension (1.7%) and hyperkalemia (1.3%). Because of this run-in design, the adverse reaction rates described below are lower than expected in practice.

In the double-blind period, safety was evaluated in 4,203 patients treated with ENTRESTO and 4,229 treated with enalapril. In PARADIGM-HF, patients randomized to ENTRESTO received treatment for up to 4.3 years, with a median duration of exposure of 24 months; 3,271 patients were treated for more than one year. Discontinuation of therapy because of an adverse event during the double-blind period occurred in 450 (10.7%) of ENTRESTO-treated patients and 516 (12.2%) of patients receiving enalapril.

Adverse reactions occurring at an incidence of greater than or equal to 5% in patients who were treated with ENTRESTO in the double-blind period of PARADIGM-HF are shown in Table 3.

In PARADIGM-HF, the incidence of angioedema was 0.1% in both the enalapril and ENTRESTO run-in periods. In the double-blind period, the incidence of angioedema was higher in patients treated with ENTRESTO than enalapril (0.5% and 0.2%, respectively). The incidence of angioedema in Black patients was 2.4% with ENTRESTO and 0.5% with enalapril [see Warnings and Precautions (5.2)].

Orthostasis was reported in 2.1% of patients treated with ENTRESTO compared to 1.1% of patients treated with enalapril during the double-blind period of PARADIGM-HF. Falls were reported in 1.9% of patients treated with ENTRESTO compared to 1.3% of patients treated with enalapril.

Table 3: Adverse Reactions Reported in greater than or equal to 5% of Patients Treated with ENTRESTO in the Double-Blind Period of PARADIGM-HF
 | ENTRESTO (n = 4,203) % | Enalapril (n = 4,229) %
Hypotension | 18 | 12
Hyperkalemia | 12 | 14
Cough | 9 | 13
Dizziness | 6 | 5
Renal failure/acute renal failure | 5 | 5

In PARAGON-HF, no new adverse reactions were identified.

Pediatric Heart Failure

The adverse reactions observed in pediatric patients 1 year to less than 18 years old who received treatment with ENTRESTO were consistent with those observed in adult patients.

Laboratory Abnormalities

Hemoglobin and Hematocrit

Decreases in hemoglobin/hematocrit of greater than 20% were observed in approximately 5% of both ENTRESTO- and enalapril-treated patients in the double-blind period in PARADIGM-HF. Decreases in hemoglobin/hematocrit of greater than 20% were observed in approximately 7% of ENTRESTO-treated patients and 9% of valsartan-treated patients in the double-blind period in PARAGON-HF.

Serum Creatinine

During the double-blind period in PARADIGM-HF, approximately 16% of both ENTRESTO- and enalapril-treated patients had increases in serum creatinine of greater than 50%. During the double-blind period in PARAGON-HF, approximately 17% of ENTRESTO-treated patients and 21% of valsartan-treated patients had increases in serum creatinine of greater than 50%.

Serum Potassium

During the double-blind period of PARADIGM-HF, approximately 16% of both ENTRESTO- and enalapril-treated patients had potassium concentrations greater than 5.5 mEq/L. During the double-blind period of PARAGON-HF, approximately 18% of ENTRESTO-treated patients and 20% of valsartan-treated patients had potassium concentrations greater than 5.5 mEq/L.

6.2 Postmarketing Experience

The following additional adverse reactions have been reported in postmarketing experience. Because these reactions are reported voluntarily from a population of uncertain size, it is not always possible to reliably estimate their frequency or establish a causal relationship to drug exposure.

Hypersensitivity including rash, pruritus, and anaphylactic reaction

7 DRUG INTERACTIONS

7.1 Dual Blockade of the Renin-Angiotensin-Aldosterone System

Concomitant use of ENTRESTO with an ACE inhibitor is contraindicated because of the increased risk of angioedema [see Contraindications (4)].

Avoid use of ENTRESTO with an ARB, because ENTRESTO contains the angiotensin II receptor blocker valsartan.

The concomitant use of ENTRESTO with aliskiren is contraindicated in patients with diabetes [see Contraindications (4)]. Avoid use with aliskiren in patients with renal impairment (eGFR less than 60 mL/min/1.73 m^2).

7.2 Potassium-Sparing Diuretics

As with other drugs that block angiotensin II or its effects, concomitant use of potassium-sparing diuretics (e.g., spironolactone, triamterene, amiloride), potassium supplements, or salt substitutes containing potassium may lead to increases in serum potassium [see Warnings and Precautions (5.5)].

7.3 Nonsteroidal Anti-Inflammatory Drugs (NSAIDs) Including Selective Cyclooxygenase-2 Inhibitors (COX-2 Inhibitors)

In patients who are elderly, volume-depleted (including those on diuretic therapy), or with compromised renal function, concomitant use of NSAIDs, including COX-2 inhibitors, with ENTRESTO may result in worsening of renal function, including possible acute renal failure. These effects are usually reversible. Monitor renal function periodically.

7.4 Lithium

Increases in serum lithium concentrations and lithium toxicity have been reported during concomitant administration of lithium with angiotensin II receptor antagonists. Monitor serum lithium levels during concomitant use with ENTRESTO.

8 USE IN SPECIFIC POPULATIONS

8.1 Pregnancy

Risk Summary

ENTRESTO can cause fetal harm when administered to a pregnant woman. Use of drugs that act on the renin-angiotensin system during the second and third trimesters of pregnancy reduces fetal renal function and increases fetal and neonatal morbidity and death (see Clinical Considerations). Most epidemiologic studies examining fetal abnormalities after exposure to antihypertensive use in the first trimester have not distinguished drugs affecting the renin-angiotensin system from other antihypertensive agents. In animal reproduction studies, ENTRESTO treatment during organogenesis resulted in increased embryo-fetal lethality in rats and rabbits and teratogenicity in rabbits (see Data). When pregnancy is detected, consider alternative drug treatment and discontinue ENTRESTO. However, if there is no appropriate alternative to therapy with drugs affecting the renin-angiotensin system, and if the drug is considered lifesaving for the mother, advise a pregnant woman of the potential risk to the fetus.

The background risk of major birth defects and miscarriage for the indicated population is unknown. All pregnancies have a background risk of birth defect, loss, or other adverse outcomes. In the U.S. general population, the estimated background risk of major birth defects and miscarriage in clinically recognized pregnancies is 2 to 4% and 15 to 20%, respectively.

Clinical Considerations

Fetal/Neonatal Adverse Reactions

Oligohydramnios in pregnant women who use drugs affecting the renin-angiotensin system in the second and third trimesters of pregnancy can result in the following: reduced fetal renal function leading to anuria and renal failure, fetal lung hypoplasia, skeletal deformations, including skull hypoplasia, hypotension, and death.

Perform serial ultrasound examinations to assess the intra-amniotic environment. Fetal testing may be appropriate, based on the week of gestation. Patients and physicians should be aware, however, that oligohydramnios may not appear until after the fetus has sustained irreversible injury. If oligohydramnios is observed, consider alternative drug treatment. Closely observe neonates with histories of in utero exposure to ENTRESTO for hypotension, oliguria, and hyperkalemia. In neonates with a history of in utero exposure to ENTRESTO, if oliguria or hypotension occurs, support blood pressure and renal perfusion. Exchange transfusions or dialysis may be required as a means of reversing hypotension and replacing renal function.

Data

Animal Data

ENTRESTO treatment during organogenesis resulted in increased embryo-fetal lethality in rats at doses greater than or equal to 49 mg sacubitril/51 mg valsartan/kg/day (less than or equal to 0.06 [LBQ657, the active metabolite] and 0.72 [valsartan]-fold the maximum recommended human dose [MRHD] of 97/103 mg twice-daily on the basis of the area under the plasma drug concentration-time curve [AUC]) and rabbits at doses greater than or equal to 5 mg sacubitril/5 mg valsartan/kg/day (2-fold and 0.03-fold the MRHD on the basis of valsartan and LBQ657 AUC, respectively). ENTRESTO is teratogenic based on a low incidence of fetal hydrocephaly, associated with maternally toxic doses, which was observed in rabbits at an ENTRESTO dose of greater than or equal to 5 mg sacubitril/5 mg valsartan/kg/day. The adverse embryo-fetal effects of ENTRESTO are attributed to the angiotensin receptor antagonist activity.

Pre- and postnatal development studies in rats at sacubitril doses up to 750 mg/kg/day (2.2-fold the MRHD on the basis of LBQ657 AUC) and valsartan at doses up to 600 mg/kg/day (0.86-fold the MRHD on the basis of AUC) indicate that treatment with ENTRESTO during organogenesis, gestation and lactation may affect pup development and survival.

8.2 Lactation

Risk Summary

There is no information regarding the presence of sacubitril/valsartan in human milk, the effects on the breastfed infant, or the effects on milk production. Sacubitril/valsartan is present in rat milk (see Data). Because of the potential for serious adverse reactions in breastfed infants from exposure to sacubitril/valsartan, advise a nursing woman that breastfeeding is not recommended during treatment with ENTRESTO.

Data

Following an oral dose (15 mg sacubitril/15 mg valsartan/kg) of [^14C] ENTRESTO to lactating rats, transfer of LBQ657 into milk was observed. After a single oral administration of 3 mg/kg [^14C] valsartan to lactating rats, transfer of valsartan into milk was observed.

8.4 Pediatric Use

The safety and effectiveness of ENTRESTO have been established for the treatment of heart failure in pediatric patients 1 year to less than 18 years. Use of ENTRESTO was evaluated in a multinational, randomized, double-blind trial comparing ENTRESTO and enalapril in 375 patients aged 1 month to less than 18 years (ENTRESTO n = 187; Enalapril n = 188) (PANORAMA-HF) [see Clinical Studies (14.2)]. The safety profile in pediatric patients (1 year to less than 18 years) receiving ENTRESTO was similar to that seen in adult patients.

Limited safety and efficacy data in patients aged 1 month to less than 1 year were inadequate to support conclusions on safety and efficacy in this age group.

Juvenile Animal Toxicity Data

Sacubitril given orally to juvenile rats from postnatal day (PND) 7 to PND 35 or PND 70 (an age approximately equivalent to neonatal through pre-pubertal development or adulthood in humans) at doses greater than or equal to 400 mg/kg/day (approximately 2-fold the AUC exposure to the active metabolite of sacubitril, LBQ657, at an ENTRESTO pediatric clinical dose of 3.1 mg/kg twice daily) resulted in decreases in body weight, bone length, and bone mass. The decrease in body weight was transient from PND 10 to PND 20 and the effects for most bone parameters were reversible after treatment stopped. Exposure at the No-Observed-Adverse-Effect-Level (NOAEL) of 100 mg/kg/day was approximately 0.5-fold the AUC exposure to LBQ657 at the 3.1 mg/kg twice daily dose of ENTRESTO. The mechanism underlying bone effects in rats and the translatability to pediatric patients are unknown.

Valsartan given orally to juvenile rats from PND 7 to PND 70 (an age approximately equivalent to neonatal through adulthood in humans) produced persistent, irreversible kidney damage at all dose levels. Exposure at the lowest tested dose of 1 mg/kg/day was approximately 0.2-fold the exposure at 3.1 mg/kg twice daily dose of ENTRESTO based on AUC. These kidney effects in neonatal rats represent expected exaggerated pharmacological effects that are observed if rats are treated during the first 13 days of life. This period coincides with 36 weeks of gestation in humans, which could occasionally extend up to 44 weeks after conception in humans. In humans, nephrogenesis is thought to be complete around birth; however, maturation of other aspects of kidney function (such as glomerular filtration and tubular function) may continue until approximately 2 years of age. It is unknown whether post-natal use of valsartan before maturation of renal function is complete has long-term deleterious effects on the kidney.

8.5 Geriatric Use

There were 4,143 and 3,971 heart failure patients 65 years of age and older in PARADIGM-HF and PARAGON-HF, respectively [see Clinical Studies (14)]. Of the total number of ENTRESTO-treated patients, 2,087 (49.6%) and 1,995 (82.9%) were 65 years of age and older, while 786 (18.7%) and 1,100 (45.7%) were 75 years of age and older in PARADIGM-HF and PARAGON-HF, respectively. No overall differences in safety or effectiveness of ENTRESTO have been observed between patients 65 years of age and older and younger adult patients in either study.

No relevant pharmacokinetic differences have been observed in elderly (≥ 65 years) or very elderly (≥ 75 years) patients compared to the overall population [see Clinical Pharmacology (12.3)].

8.6 Hepatic Impairment

No dose adjustment is required when administering ENTRESTO to patients with mild hepatic impairment (Child-Pugh A classification). Half of the starting dose is recommended in adult and pediatric patients with heart failure and with moderate hepatic impairment (Child-Pugh B classification). The use of ENTRESTO in patients with severe hepatic impairment (Child-Pugh C classification) is not recommended, as no studies have been conducted in these patients [see Dosage and Administration (2.8) and Clinical Pharmacology (12.3)].

8.7 Renal Impairment

No dose adjustment is required in patients with mild (eGFR 60 to 90 mL/min/1.73 m^2) to moderate (eGFR 30 to 60 mL/min/1.73 m^2) renal impairment. Half of the starting dose is recommended in adult and pediatric patients with heart failure and with severe renal impairment (eGFR less than 30 mL/min/1.73 m^2). [see Dosage and Administration (2.7), Warnings and Precautions (5.4) and Clinical Pharmacology (12.3)].

10 OVERDOSAGE

Limited data are available with regard to overdosage in human subjects with ENTRESTO. In healthy volunteers, a single dose of ENTRESTO 583 mg sacubitril/617 mg valsartan, and multiple doses of 437 mg sacubitril/463 mg valsartan (14 days) have been studied and were well tolerated.

Hypotension is the most likely result of overdosage due to the blood pressure lowering effects of ENTRESTO. Symptomatic treatment should be provided.

ENTRESTO is unlikely to be removed by hemodialysis because of high protein binding.

11 DESCRIPTION

ENTRESTO (sacubitril and valsartan) is a combination of a neprilysin inhibitor and an angiotensin II receptor blocker.

ENTRESTO contains a complex comprised of anionic forms of sacubitril and valsartan, sodium cations, and water molecules in the molar ratio of 1:1:3:2.5, respectively. Following oral administration, the complex dissociates into sacubitril (which is further metabolized to LBQ657) and valsartan. The complex is chemically described as Octadecasodiumhexakis(4-{[(1S,3R)-1-([1,1´-biphenyl]-4-ylmethyl)-4-ethoxy-3-methyl-4-oxobutyl]amino}-4-oxobutanoate)hexakis(N-pentanoyl-N-{[2´-(1H-tetrazol-1-id-5-yl)[1,1´-biphenyl]-4-yl]methyl}-L-valinate)—water (1/15).

Its empirical formula (hemipentahydrate) is C48H55N6O8Na3 2.5 H2O. Its molecular mass is 957.99 g/mol and its schematic structural formula is:

ENTRESTO is available as film-coated tablets for oral administration, containing 24 mg of sacubitril and 26 mg of valsartan; 49 mg of sacubitril and 51 mg of valsartan; and 97 mg of sacubitril and 103 mg of valsartan. The tablet inactive ingredients are colloidal silicon dioxide, crospovidone, low-substituted hydroxypropylcellulose, magnesium stearate (vegetable origin), microcrystalline cellulose, and talc. The film-coat inactive ingredients are hypromellose, iron oxide red (E172), polyethylene glycol 4000, talc, and titanium dioxide (E171). The film-coat for the 24 mg of sacubitril and 26 mg of valsartan tablet and the 97 mg of sacubitril and 103 mg of valsartan tablet also contains iron oxide black (E172). The film-coat for the 49 mg of sacubitril and 51 mg of valsartan tablet contains iron oxide yellow (E172).

ENTRESTO SPRINKLE is available as film-coated oral pellets within capsules for oral administration, containing 6 mg of sacubitril and 6 mg of valsartan; and 15 mg of sacubitril and 16 mg of valsartan. The oral pellet inactive ingredients are colloidal silicon dioxide, hydroxypropylcellulose, magnesium stearate (vegetable origin), microcrystalline cellulose, and talc. The film-coat inactive ingredients are basic butylated methacrylate copolymer, sodium lauryl sulfate, stearic acid, and talc. The capsule shell inactive ingredients are hypromellose and titanium dioxide (E171). The capsule shell for the 15 mg of sacubitril and 16 mg of valsartan oral pellets also contains iron oxide yellow (E172). The printing ink contains shellac, propylene glycol, iron oxide red (E172), ammonia solution (concentrated), and potassium hydroxide.

12 CLINICAL PHARMACOLOGY

12.1 Mechanism of Action

ENTRESTO contains a neprilysin inhibitor, sacubitril, and an angiotensin receptor blocker, valsartan. ENTRESTO inhibits neprilysin (neutral endopeptidase; NEP) via LBQ657, the active metabolite of the prodrug sacubitril, and blocks the angiotensin II type-1 (AT1) receptor via valsartan. The cardiovascular and renal effects of ENTRESTO in heart failure patients are attributed to the increased levels of peptides that are degraded by neprilysin, such as natriuretic peptides, by LBQ657, and the simultaneous inhibition of the effects of angiotensin II by valsartan. Valsartan inhibits the effects of angiotensin II by selectively blocking the AT1 receptor, and also inhibits angiotensin II-dependent aldosterone release.

12.2 Pharmacodynamics

The pharmacodynamic effects of ENTRESTO were evaluated after single and multiple dose administrations in healthy subjects and in patients with heart failure, and are consistent with simultaneous neprilysin inhibition and renin-angiotensin system blockade.

In a 7-day valsartan-controlled study in patients with reduced ejection fraction (HFrEF), administration of ENTRESTO resulted in a significant non-sustained increase in natriuresis, increased urine cGMP, and decreased plasma MR-proANP and NT-proBNP compared to valsartan.

In a 21-day study in HFrEF patients, ENTRESTO significantly increased urine ANP and cGMP and plasma cGMP, and decreased plasma NT-proBNP, aldosterone and endothelin-1. ENTRESTO also blocked the AT1-receptor as evidenced by increased plasma renin activity and plasma renin concentrations. In PARADIGM-HF, ENTRESTO decreased plasma NT-proBNP (not a neprilysin substrate) and increased plasma BNP (a neprilysin substrate) and urine cGMP compared with enalapril.

In PARAMOUNT, a randomized, double-blind, 36-week study in patients with heart failure with LVEF greater than or equal to 45% comparing 97/103 mg of ENTRESTO (n=149) to 160 mg of valsartan (n =152) twice-daily, ENTRESTO decreased NT-proBNP by 17% while valsartan increased NT-proBNP by 8% at Week 12 (p = 0.005).

In PARAGON-HF, ENTRESTO decreased NT-proBNP by 24% (Week 16) and 19% (Week 48) compared to 6% and 3% reductions on valsartan, respectively.

In PANORAMA-HF, a reduction in NT-proBNP was observed at Weeks 4 and 12 for ENTRESTO (40% and 50%) compared to baseline. The NT-proBNP levels continued to decrease over the duration of the study with a reduction of 65% for ENTRESTO at Week 52 compared to baseline.

QT Prolongation: In a thorough QTc clinical study in healthy male subjects, single doses of ENTRESTO 194 mg sacubitril/206 mg valsartan and 583 mg sacubitril/617 mg valsartan had no effect on cardiac repolarization.

Amyloid-β: Neprilysin is one of multiple enzymes involved in the clearance of amyloid-β (Aβ) from the brain and cerebrospinal fluid (CSF). Administration of ENTRESTO 194 mg sacubitril/206 mg valsartan once-daily for 2 weeks to healthy subjects was associated with an increase in CSF Aβ1-38 compared to placebo; there were no changes in concentrations of CSF Aβ1-40 or CSF Aβ1-42. The clinical relevance of this finding is unknown [see Nonclinical Toxicology (13)].

Blood Pressure: Addition of a 50 mg single dose of sildenafil to ENTRESTO at steady state (194 mg sacubitril/206 mg valsartan once daily for 5 days) in patients with hypertension was associated with additional blood pressure (BP) reduction (approximately 5/4 mmHg, systolic/diastolic BP) compared to administration of ENTRESTO alone.

Co-administration of ENTRESTO did not significantly alter the BP effect of intravenous nitroglycerin.

12.3 Pharmacokinetics

Absorption

Following oral administration, ENTRESTO dissociates into sacubitril and valsartan. Sacubitril is further metabolized to LBQ657. The peak plasma concentrations of sacubitril, LBQ657, and valsartan are reached in 0.5 hours, 2 hours, and 1.5 hours, respectively. The oral absolute bioavailability of sacubitril is estimated to be greater than or equal to 60%. The valsartan in ENTRESTO is more bioavailable than the valsartan in other marketed tablet formulations; 26 mg, 51 mg, and 103 mg of valsartan in ENTRESTO is equivalent to 40 mg, 80 mg, and 160 mg of valsartan in other marketed tablet formulations, respectively.

Following twice-daily dosing of ENTRESTO, steady-state levels of sacubitril, LBQ657, and valsartan are reached in 3 days. At steady state, sacubitril and valsartan do not accumulate significantly, whereas LBQ657 accumulates by 1.6-fold. ENTRESTO administration with food has no clinically significant effect on the systemic exposures of sacubitril, LBQ657, or valsartan. Although there is a decrease in exposure to valsartan when ENTRESTO is administered with food, this decrease is not accompanied by a clinically significant reduction in the therapeutic effect. ENTRESTO can therefore be administered with or without food.

Distribution

Sacubitril, LBQ657 and valsartan are highly bound to plasma proteins (94% to 97%). Based on the comparison of plasma and CSF exposures, LBQ657 crosses the blood brain barrier to a limited extent (0.28%). The average apparent volumes of distribution of valsartan and sacubitril are 75 and 103 L, respectively.

Metabolism

Sacubitril is readily converted to LBQ657 by esterases; LBQ657 is not further metabolized to a significant extent. Valsartan is minimally metabolized; only about 20% of the dose is recovered as metabolites. A hydroxyl metabolite has been identified in plasma at low concentrations (less than 10%).

Elimination

Following oral administration, 52% to 68% of sacubitril (primarily as LBQ657) and approximately 13% of valsartan and its metabolites are excreted in urine; 37% to 48% of sacubitril (primarily as LBQ657), and 86% of valsartan and its metabolites are excreted in feces. Sacubitril, LBQ657, and valsartan are eliminated from plasma with a mean elimination half-life (T1/2) of approximately 1.4 hours, 11.5 hours, and 9.9 hours, respectively.

Linearity/Nonlinearity

The pharmacokinetics of sacubitril, LBQ657, and valsartan were linear over an ENTRESTO dose range of 24 mg sacubitril/26 mg valsartan to 194 mg sacubitril/206 mg valsartan.

Drug Interactions:

Effect of Co-administered Drugs on ENTRESTO:

Because CYP450 enzyme-mediated metabolism of sacubitril and valsartan is minimal, coadministration with drugs that impact CYP450 enzymes is not expected to affect the pharmacokinetics of ENTRESTO. Dedicated drug interaction studies demonstrated that coadministration of furosemide, warfarin, digoxin, carvedilol, a combination of levonorgestrel/ethinyl estradiol, amlodipine, omeprazole, hydrochlorothiazide (HCTZ), metformin, atorvastatin, and sildenafil, did not alter the systemic exposure to sacubitril, LBQ657 or valsartan.

Effect of ENTRESTO on Co-administered Drugs:

In vitro data indicate that sacubitril inhibits OATP1B1 and OATP1B3 transporters. The effects of ENTRESTO on the pharmacokinetics of coadministered drugs are summarized in Figure 1.

Figure 1: Effect of ENTRESTO on Pharmacokinetics of Coadministered Drugs

Specific Populations

Effect of specific populations on the pharmacokinetics of LBQ657 and valsartan are shown in Figure 2.

Figure 2: Pharmacokinetics of ENTRESTO in Specific Populations

Note: Child-Pugh Classification was used for hepatic impairment.

Pediatric Patients: The pharmacokinetics of ENTRESTO were evaluated in pediatric heart failure patients 1 to less than 18 years old administered oral doses of 0.8 mg/kg and 3.1 mg/kg of ENTRESTO. Pharmacokinetic data indicated that exposure to ENTRESTO in pediatric and adult patients is similar.

13 NONCLINICAL TOXICOLOGY

13.1 Carcinogenesis, Mutagenesis, Impairment of Fertility

Carcinogenesis and Mutagenesis

Carcinogenicity studies conducted in mice and rats with sacubitril and valsartan did not identify any carcinogenic potential for ENTRESTO. The LBQ657 Cmax at the high dose (HD) of 1200 mg/kg/day in male and female mice was, respectively, 14 and 16 times that in humans at the MRHD. The LBQ657 Cmax in male and female rats at the HD of 400 mg/kg/day was, respectively, 1.7 and 3.5 times that at the MRHD. The doses of valsartan studied (high dose of 160 and 200 mg/kg/day in mice and rats, respectively) were about 4 and 10 times, respectively, the MRHD on a mg/m^2 basis.

Mutagenicity and clastogenicity studies conducted with ENTRESTO, sacubitril, and valsartan did not reveal any effects at either the gene or chromosome level.

Impairment of Fertility

ENTRESTO did not show any effects on fertility in rats up to a dose of 73 mg sacubitril/77 mg valsartan/kg/day (≤ 1.0-fold and ≤ 0.18-fold the MRHD on the basis of the AUCs of valsartan and LBQ657, respectively).

13.2 Animal Toxicology and/or Pharmacology

The effects of ENTRESTO on amyloid-β concentrations in CSF and brain tissue were assessed in young (2 to 4 years old) cynomolgus monkeys treated with ENTRESTO (24 mg sacubitril/26 mg valsartan/kg/day) for 2 weeks. In this study, ENTRESTO affected CSF Aβ clearance, increasing CSF Aβ 1-40, 1-42, and 1-38 levels in CSF; there was no corresponding increase in Aβ levels in the brain. In addition, in a toxicology study in cynomolgus monkeys treated with ENTRESTO at 146 mg sacubitril/154 mg valsartan/kg/day for 39-weeks, there was no amyloid-β accumulation in the brain.

14 CLINICAL STUDIES

Dosing in clinical trials was based on the total amount of both components of ENTRESTO, i.e., 24/26 mg, 49/51 mg, and 97/103 mg were referred to as 50 mg, 100 mg, and 200 mg, respectively.

14.1 Adult Heart Failure

PARADIGM-HF

PARADIGM-HF was a multinational, randomized, double-blind trial comparing ENTRESTO and enalapril in 8,442 adult patients with symptomatic chronic heart failure (NYHA class II–IV) and systolic dysfunction (left ventricular ejection fraction ≤ 40%). Patients had to have been on an ACE inhibitor or ARB for at least four weeks and on maximally tolerated doses of beta-blockers. Patients with a systolic blood pressure of less than 100 mmHg at screening were excluded.

The primary objective of PARADIGM-HF was to determine whether ENTRESTO, a combination of sacubitril and an RAS inhibitor (valsartan), was superior to an RAS inhibitor (enalapril) alone in reducing the risk of the combined endpoint of cardiovascular (CV) death or hospitalization for heart failure (HF).

After discontinuing their existing ACE inhibitor or ARB therapy, patients entered sequential single-blind run-in periods during which they received enalapril 10 mg twice-daily, followed by ENTRESTO 100 mg twice-daily, increasing to 200 mg twice-daily. Patients who successfully completed the sequential run-in periods were randomized to receive either ENTRESTO 200 mg (N = 4,209) twice-daily or enalapril 10 mg (N = 4,233) twice-daily. The primary endpoint was the first event in the composite of CV death or hospitalization for HF. The median follow-up duration was 27 months and patients were treated for up to 4.3 years.

The population was 66% Caucasian, 18% Asian, and 5% Black; the mean age was 64 years and 78% were male. At randomization, 70% of patients were NYHA Class II, 24% were NYHA Class III, and 0.7% were NYHA Class IV. The mean left ventricular ejection fraction was 29%. The underlying cause of heart failure was coronary artery disease in 60% of patients; 71% had a history of hypertension, 43% had a history of myocardial infarction, 37% had an eGFR less than 60 mL/min/1.73m^2, and 35% had diabetes mellitus. Most patients were taking beta-blockers (94%), mineralocorticoid antagonists (58%), and diuretics (82%). Few patients had an implantable cardioverter-defibrillator (ICD) or cardiac resynchronization therapy-defibrillator (CRT-D) (15%).

PARADIGM-HF demonstrated that ENTRESTO, a combination of sacubitril and an RAS inhibitor (valsartan), was superior to a RAS inhibitor (enalapril), in reducing the risk of the combined endpoint of cardiovascular death or hospitalization for heart failure, based on a time-to-event analysis (hazard ratio [HR] 0.80; 95% confidence interval [CI], 0.73, 0.87, p < 0.0001). The treatment effect reflected a reduction in both cardiovascular death and heart failure hospitalization; see Table 4 and Figure 3. Sudden death accounted for 45% of cardiovascular deaths, followed by pump failure, which accounted for 26%.

ENTRESTO also improved overall survival (HR 0.84; 95% CI [0.76, 0.93], p = 0.0009) (Table 4). This finding was driven entirely by a lower incidence of cardiovascular mortality on ENTRESTO.

Table 4: Treatment Effect for the Primary Composite Endpoint, Its Components, and All-cause Mortality in PARADIGM-HF
 | ENTRESTO N = 4,187 n (%) | Enalapril N = 4,212 n (%) | Hazard Ratio (95% CI) | p-value
Primary composite endpoint of cardiovascular death or heart failure hospitalization | 914 (21.8) | 1,117 (26.5) | 0.80 (0.73, 0.87) | < 0.0001
Cardiovascular death as first event | 377 (9.0) | 459 (10.9)
Heart failure hospitalization as first event | 537 (12.8) | 658 (15.6)
Number of patients with events:*
Cardiovascular death** | 558 (13.3) | 693 (16.5) | 0.80 (0.71, 0.89)
Heart failure hospitalizations | 537 (12.8) | 658 (15.6) | 0.79 (0.71, 0.89)
All-cause mortality | 711 (17.0) | 835 (19.8) | 0.84 (0.76, 0.93) | 0.0009
*Analyses of the components of the primary composite endpoint were not prospectively planned to be adjusted for multiplicity.
**Includes patients who had heart failure hospitalization prior to death.

The Kaplan-Meier curves presented below (Figure 3) show time to first occurrence of the primary composite endpoint (3A), and time to occurrence of cardiovascular death at any time (3B) and first heart failure hospitalization (3C).

Figure 3: Kaplan-Meier Curves for the Primary Composite Endpoint (A), Cardiovascular Death (B), and Heart Failure Hospitalization (C)

A wide range of demographic characteristics, baseline disease characteristics, and baseline concomitant medications were examined for their influence on outcomes. The results of the primary composite endpoint were consistent across the subgroups examined (Figure 4).

Figure 4: Primary Composite Endpoint (CV Death or HF Hospitalization) - Subgroup Analysis (PARADIGM-HF)

Note: The figure above presents effects in various subgroups, all of which are baseline characteristics. The 95% confidence limits that are shown do not take into account the number of comparisons made, and may not reflect the effect of a particular factor after adjustment for all other factors. Apparent homogeneity or heterogeneity among groups should not be over-interpreted.

PARAGON-HF

PARAGON-HF, was a multicenter, randomized, double-blind trial comparing ENTRESTO and valsartan in 4,796 adult patients with symptomatic heart failure with left ventricular ejection fraction greater than or equal to 45%, and structural heart disease [either left atrial enlargement (LAE) or left ventricular hypertrophy (LVH)]. Patients with a systolic blood pressure of less than 110 mmHg and patients with any prior echocardiographic LVEF less than 40% at screening were excluded.

The primary objective of PARAGON-HF was to determine whether ENTRESTO reduced the rate of the composite endpoint of total (first and recurrent) heart failure (HF) hospitalizations and cardiovascular (CV) death.

After discontinuing their existing ACE inhibitor or ARB therapy, patients entered sequential single-blind run-in periods during which they received valsartan 80 mg twice-daily, followed by ENTRESTO 100 mg twice-daily. Patients on prior low doses of an ACEi or ARB began the run-in period receiving valsartan 40 mg twice-daily for 1 to 2 weeks. Patients who successfully completed the sequential run-in periods were randomized to receive either ENTRESTO 200 mg (N = 2,419) twice-daily or valsartan 160 mg (N = 2,403) twice-daily. The median follow-up duration was 35 months and patients were treated for up to 4.7 years.

The population was 81% Caucasian, 13% Asian, and 2% Black; the mean age was 73 years and 52% were female. At randomization, 77% of patients were NYHA Class II, 19% were NYHA Class III, and 0.4% were NYHA Class IV. The median left ventricular ejection fraction was 57%. The underlying cause of heart failure was of ischemic etiology in 36% of patients. Furthermore, 96% had a history of hypertension, 23% had a history of myocardial infarction, 46% had an eGFR less than 60 mL/min/1.73 m^2, and 43% had diabetes mellitus. Most patients were taking beta-blockers (80%) and diuretics (95%).

PARAGON-HF demonstrated that ENTRESTO had a numerical reduction in the rate of the composite endpoint of total (first and recurrent) HF hospitalizations and CV death, based on an analysis using a proportional rates model (rate ratio [RR] 0.87; 95% CI [0.75, 1.01], p = 0.06); see Table 5. The treatment effect was primarily driven by the reduction in total HF hospitalizations in patients randomized to ENTRESTO (RR 0.85; 95% CI [0.72, 1.00]).

Table 5: Treatment Effect for the Primary Composite Endpoint and Its Components in PARAGON-HF
 | ENTRESTO N = 2,407 |  | Valsartan N = 2,389 |  | Effect Size (95% CI)
Efficacy Endpoints | n | Event Ratea | n | Event Ratea
Composite of total (first and recurrent) HF hospitalizations and CV death | 894 | 12.8 | 1,009 | 14.6 | RR = 0.87 (0.75, 1.01) p-value 0.06
Total HF Hospitalizations | 690 | 9.9 | 797 | 11.6 | RR = 0.85 (0.72, 1.00)
CV Deathb | 204 | 2.9 | 212 | 3.1 | HR = 0.95 (0.79, 1.16)
Abbreviations: RR = rate ratio, HR = hazard ratio.
aEvent rate per 100 patient-years.
bIncludes patients who had CV death following HF hospitalization event.

Figure 5 shows the mean number of composite endpoint events of total HF hospitalizations and CV death over time.

Figure 5: Mean Number of Events Over Time for the Primary Composite Endpoint of Total HF Hospitalizations and CV Death

A wide range of demographic characteristics, baseline disease characteristics, and baseline concomitant medications were examined for their influence on outcomes (Figure 6).

Figure 6: Primary Composite Endpoint of Total HF Hospitalizations and CV Death – Subgroup Analysis (PARAGON-HF)

Note: The figure above presents effects in various subgroups, all of which are baseline characteristics. The 95% confidence limits that are shown do not take into account the number of comparisons made, and may not reflect the effect of a particular factor after adjustment for all other factors.

In an analysis of the relationship between LVEF and outcome in PARADIGM-HF and PARAGON-HF, patients with LVEF below normal treated with ENTRESTO experienced greater risk reduction (Figure 7).

Figure 7: Treatment Effect for the Composite Endpoint of Time to First HF Hospitalization or CV Death by LVEF in PARADIGM-HF and PARAGON-HF

14.2 Pediatric Heart Failure

The efficacy of ENTRESTO was evaluated in a multinational, randomized, double-blind trial PANORAMA-HF comparing ENTRESTO (n = 187) and enalapril (n = 188) in pediatric patients aged 1 month to less than 18 years old due to systemic left ventricular systolic dysfunction (LVEF ≤ 45% or fractional shortening ≤ 22.5%). Patients with systemic right ventricle, single ventricle, restrictive cardiomyopathy or hypertrophic cardiomyopathy were excluded from the trial. Efficacy of ENTRESTO in patients less than 1 year old was not established. At Week 52, there were 144 ENTRESTO and 133 enalapril patients with a post-baseline assessment of NT-proBNP. The estimated least squares mean percent reduction from baseline in NT-proBNP was 65% and 62% in the ENTRESTO and enalapril groups, respectively. While the between-group difference was not nominally statistically significant, the reductions for ENTRESTO and enalapril were larger than what was seen in adults; these reductions did not appear to be attributable to post-baseline changes in background therapy.

Because ENTRESTO improved outcomes and reduced NT-proBNP in adults in PARADIGM-HF, the effect on NT-proBNP was the basis to infer improved cardiovascular outcomes in pediatric patients.

16 HOW SUPPLIED/STORAGE AND HANDLING

ENTRESTO (sacubitril/valsartan) tablets are unscored, ovaloid, biconvex, and film-coated.

ENTRESTO film-coated oral pellets are round, biconvex in shape, and provided in a hard capsule.

All strengths are packaged in bottles as described below.

ENTRESTO Tablets
Sacubitril/valsartan mg/mg | Color | Debossment Side 1/side 2 | NDC 0078-XXXX-XX
 |  |  | Bottle of 60 | Bottle of 180
24/26 | Violet white | NVR/LZ | 0659-20 | 0659-67
49/51 | Pale yellow | NVR/L1 | 0777-20 | 0777-67
97/103 | Light pink | NVR/L11 | 0696-20 | 0696-67
ENTRESTO SPRINKLE
Sacubitril/valsartan mg/mg | Color | Print | NDC 0078-XXXX-XX
 |  |  | Bottle of 60
6/6 | White cap and transparent body | “NVR” and both parts with arrows and “04” | 1231-20
15/16 | Yellow cap and transparent body | “NVR” and both parts with arrows and “10” | 1238-20

STORAGE AND HANDLING

Store at 20°C to 25°C (68°F to 77°F), excursions permitted between 15°C and 30°C (59°F and 86°F) [see USP Controlled Room Temperature]. Protect from moisture.

17 PATIENT COUNSELING INFORMATION

Advise patients to read the FDA-approved patient labeling (Patient Information and Instructions for Use).

Pregnancy: Advise female patients of childbearing age about the consequences of exposure to ENTRESTO during pregnancy. Discuss treatment options with women planning to become pregnant. Ask patients to report pregnancies to their physicians as soon as possible [see Warnings and Precautions (5.1) and Use in Specific Populations (8.1)].

Lactation: Advise patients that breastfeeding is not recommended during treatment with ENTRESTO [see Use in Specific Populations (8.2)].

Angioedema: Advise patients to discontinue use of their previous ACE inhibitor or ARB. Advise patients to allow a 36-hour wash-out period if switching from or to an ACE inhibitor [see Contraindications (4) and Warnings and Precautions (5.2)].

Administering ENTRESTO SPRINKLE oral pellets: Advise patients to read and follow the Instructions for Use for ENTRESTO SPRINKLE.

Distributed by:
Novartis Pharmaceuticals Corporation
East Hanover, New Jersey 07936

© Novartis

T2024-28

PATIENT INFORMATION

ENTRESTO (en-TRESS-toh)
(sacubitril and valsartan)
tablets, for oral use

ENTRESTO SPRINKLE (en-TRESS-toh SPRINK-el)
(sacubitril and valsartan)
oral pellets

What is the most important information I should know about ENTRESTO or ENTRESTO SPRINKLE?
ENTRESTO or ENTRESTO SPRINKLE can harm or cause death to your unborn baby. Talk to your doctor about other ways to treat heart failure if you plan to become pregnant. Tell your doctor right away if you become pregnant during treatment with ENTRESTO or ENTRESTO SPRINKLE.

What is ENTRESTO or ENTRESTO SPRINKLE?
ENTRESTO or ENTRESTO SPRINKLE is a prescription medicine used to treat:

- adults with long-lasting (chronic) heart failure to help reduce the risk of death and hospitalization. ENTRESTO or ENTRESTO SPRINKLE works better when the heart cannot pump a normal amount of blood to the body.
- certain children 1 year of age and older who have symptomatic heart failure.

It is not known if ENTRESTO or ENTRESTO SPRINKLE is safe and effective in children under 1 year of age.

Do not take ENTRESTO or ENTRESTO SPRINKLE if you:

- are allergic to any of the ingredients in ENTRESTO or ENTRESTO SPRINKLE. See the end of this Patient Information leaflet for a complete list of ingredients in ENTRESTO or ENTRESTO SPRINKLE.
- have had an allergic reaction, including swelling of your face, lips, tongue, throat, or trouble breathing while taking a type of medicine called an angiotensin-converting enzyme (ACE) inhibitor or angiotensin II receptor blocker (ARB).
- take an ACE inhibitor medicine. Do not take ENTRESTO or ENTRESTO SPRINKLE for at least 36 hours before or after you take an ACE inhibitor medicine. Talk with your doctor or pharmacist before taking ENTRESTO or ENTRESTO SPRINKLE if you are not sure if you take an ACE inhibitor medicine.
- have diabetes and take a medicine that contains aliskiren.

Before taking ENTRESTO or ENTRESTO SPRINKLE, tell your doctor about all of your medical conditions, including if you:

- have a history of hereditary angioedema
- have kidney or liver problems
- have diabetes
- are pregnant or plan to become pregnant. See “What is the most important information I should know about ENTRESTO or ENTRESTO SPRINKLE?”
- are breastfeeding or plan to breastfeed. It is not known if ENTRESTO or ENTRESTO SPRINKLE passes into your breast milk. You should not breastfeed during treatment with ENTRESTO or ENTRESTO SPRINKLE. You and your doctor should decide if you will take ENTRESTO or ENTRESTO SPRINKLE or breastfeed.

Tell your doctor about all the medicines you take, including prescription and over-the-counter medicines, vitamins, and herbal supplements. Taking ENTRESTO or ENTRESTO SPRINKLE with certain other medicines may affect each other. Taking ENTRESTO or ENTRESTO SPRINKLE with other medicines can cause serious side effects. Especially tell your doctor if you take:

- potassium supplements or a salt substitute
- nonsteroidal anti-inflammatory drugs (NSAIDs)
- lithium
- other medicines for high blood pressure or heart problems, such as an ACE inhibitor, ARB, or aliskiren

Keep a list of your medicines to show your doctor and pharmacist when you get a new medicine.

How should I take ENTRESTO or ENTRESTO SPRINKLE?

- Take ENTRESTO or ENTRESTO SPRINKLE exactly as your doctor tells you to take it.
- Take ENTRESTO or ENTRESTO SPRINKLE 2 times each day. Your doctor may change your dose of ENTRESTO or ENTRESTO SPRINKLE during treatment.
- If you or your child cannot swallow tablets, or if tablets are not available in the prescribed strength, you or your child may take ENTRESTO tablets prepared as a liquid (oral) suspension or may take ENTRESTO SPRINKLE.
- If you or your child switches between taking ENTRESTO and the liquid suspension prepared from ENTRESTO tablets, or to ENTRESTO SPRINKLE, your doctor will adjust the dose as needed.
- If you or your child are prescribed ENTRESTO tablets to be prepared as a liquid suspension:
  - Your pharmacist will prepare ENTRESTO tablets for you or your child to take as a liquid suspension.
  - Shake the bottle of suspension well before measuring the dose of medicine and before taking or giving the dose.
- If you or your child are prescribed ENTRESTO SPRINKLE:
  - ENTRESTO SPRINKLE contains oral pellets inside of a capsule that must be opened and sprinkled onto 1 to 2 teaspoonfuls of soft food and taken right away.
  - Do not swallow the capsules.
  - Do not chew or crush the oral pellets.
  - See the detailed Instructions for Use information on how to take or give a dose of ENTRESTO SPRINKLE.
- If you miss a dose, take it as soon as you remember. If it is close to your next dose, do not take the missed dose. Take the next dose at your regular time.
- If you take too much ENTRESTO or ENTRESTO SPRINKLE, call your doctor right away.

What are the possible side effects of ENTRESTO or ENTRESTO SPRINKLE?
ENTRESTO or ENTRESTO SPRINKLE may cause serious side effects, including:

- See “What is the most important information I should know about ENTRESTO or ENTRESTO SPRINKLE?”
- Serious allergic reactions causing swelling of your face, lips, tongue, and throat (angioedema) that may cause trouble breathing and death. Get emergency medical help right away if you have symptoms of angioedema or trouble breathing. Do not take ENTRESTO or ENTRESTO SPRINKLE again if you have had angioedema during treatment with ENTRESTO or ENTRESTO SPRINKLE.
  People who are Black and take ENTRESTO or ENTRESTO SPRINKLE may have a higher risk of having angioedema than people who are not Black and take ENTRESTO or ENTRESTO SPRINKLE.
  People who have had angioedema before taking ENTRESTO or ENTRESTO SPRINKLE may have a higher risk of having angioedema than people who have not had angioedema before taking ENTRESTO or ENTRESTO SPRINKLE. See “Who should not take ENTRESTO or ENTRESTO SPRINKLE?”
- Low blood pressure (hypotension). Low blood pressure is common during treatment with ENTRESTO or ENTRESTO SPRINKLE. Your risk of low blood pressure is greater if you also take water pills (diuretics). Call your doctor if you become dizzy or lightheaded, or you develop extreme tiredness (fatigue).
- Kidney problems. Kidney problems are common during treatment with ENTRESTO or ENTRESTO SPRINKLE and can be serious and can lead to kidney failure. Your doctor will check your kidney function during your treatment with ENTRESTO or ENTRESTO SPRINKLE.
- Increased amount of potassium in your blood (hyperkalemia). Increased blood potassium levels are common during treatment with ENTRESTO or ENTRESTO SPRINKLE. Your doctor will check your potassium blood level during your treatment with ENTRESTO or ENTRESTO SPRINKLE.

The most common side effects of ENTRESTO or ENTRESTO SPRINKLE also include cough and dizziness.
Your doctor may need to lower your dose, temporarily stop treatment, or permanently stop treatment if you develop certain side effects or if you have changes in your kidney function or increased blood levels of potassium during treatment with ENTRESTO or ENTRESTO SPRINKLE.
These are not all of the possible side effects of ENTRESTO or ENTRESTO SPRINKLE. Call your doctor for medical advice about side effects. You may report side effects to FDA at 1-800-FDA-1088.

How should I store ENTRESTO or ENTRESTO SPRINKLE?

- Store ENTRESTO tablets or ENTRESTO SPRINKLE oral pellets at room temperature between 68°F to 77°F (20°C to 25°C).
- Protect ENTRESTO tablets or ENTRESTO SPRINKLE oral pellets from moisture.
- Store bottles of ENTRESTO tablets prepared as an oral suspension at room temperature less than 77°F (25°C) for up to 15 days. Do not refrigerate ENTRESTO tablets prepared as an oral suspension.

Keep ENTRESTO, ENTRESTO SPRINKLE and all medicines out of the reach of children.

General information about the safe and effective use of ENTRESTO or ENTRESTO SPRINKLE.
Medicines are sometimes prescribed for purposes other than those listed in a Patient Information leaflet. Do not use ENTRESTO or ENTRESTO SPRINKLE for a condition for which it was not prescribed. Do not give ENTRESTO or ENTRESTO SPRINKLE to other people, even if they have the same symptoms that you have. It may harm them. You can ask your pharmacist or doctor for information about ENTRESTO or ENTRESTO SPRINKLE that is written for health professionals.

What are the ingredients in ENTRESTO or ENTRESTO SPRINKLE?
Active ingredients: sacubitril and valsartan
ENTRESTO tablets inactive ingredients: colloidal silicon dioxide, crospovidone, low-substituted hydroxypropylcellulose, magnesium stearate (vegetable origin), microcrystalline cellulose, and talc. Film coat: hypromellose, iron oxide red (E172), polyethylene glycol 4000, talc, and titanium dioxide (E171). The film-coat for the 24 mg of sacubitril and 26 mg of valsartan tablet and the 97 mg of sacubitril and 103 mg of valsartan tablet also contains iron oxide black (E172). The film-coat for the 49 mg of sacubitril and 51 mg of valsartan tablet contains iron oxide yellow (E172).
Prepared ENTRESTO oral suspension also contains Ora-Sweet SF and Ora-Plus.
ENTRESTO SPRINKLE oral pellets inactive ingredients: colloidal silicon dioxide, hydroxypropylcellulose, magnesium stearate (vegetable origin), microcrystalline cellulose, and talc. Film-coat: basic butylated methacrylate copolymer, sodium lauryl sulfate, stearic acid, and talc. Capsule shell contains hypromellose and titanium dioxide (E171). The capsule shell for 15 mg of sacubitril and 16 mg of valsartan oral pellets also contains iron oxide yellow (E172). Printing ink: shellac, propylene glycol, iron oxide red (E172), ammonia solution (concentrated), and potassium hydroxide.
Distributed by: Novartis Pharmaceuticals Corporation East Hanover, New Jersey 07936
© Novartis
ENTRESTO is a registered trademark of Novartis AG
For more information, go to www.ENTRESTO.com or call 1-888-368-7378 (1-888-ENTRESTO).

This Patient Information has been approved by the U.S. Food and Drug Administration.

Revised: April 2024

T2024-29

INSTRUCTIONS FOR USE
ENTRESTO® SPRINKLE [en-TRESS-toh SPRINK-el]
(sacubitril and valsartan)
oral pellets
This Instructions for Use contains information on how to take or give ENTRESTO SPRINKLE.
Read this Instructions for Use before you or your child start taking ENTRESTO SPRINKLE, and each time you get a refill. There may be new information. This information does not take the place of talking to your doctor about your or your child’s medical condition or treatment.
Ask your doctor or pharmacist if you have any questions about how to take or give ENTRESTO SPRINKLE.
Important Information You Need to Know Before Taking or Giving ENTRESTO SPRINKLE.
- ENTRESTO SPRINKLE contains oral pellets inside of a capsule.
  - The capsule must be opened and the oral pellets inside must be sprinkled on soft food before you take or give ENTRESTO SPRINKLE.
  - Do not swallow the capsule or the empty capsule shells.
- Do not chew or crush the oral pellets.
- Use all of the oral pellets in the capsule. Do not use part of a capsule to try to prepare a dose.
- Do not take or give ENTRESTO SPRINKLE through a nasogastric tube (NG Tube), gastrostomy tube (G Tube), or other feeding tubes because it may clog the tube.
- ENTRESTO SPRINKLE is available in 2 strengths: 6 mg/6 mg (sacubitril 6 mg and valsartan 6 mg) and 15 mg/16 mg (sacubitril 15 mg and valsartan 16 mg).
- You can see the difference between the 2 strengths by the color of the capsule cap and the imprint on it.
  - The capsule containing the 6 mg/6 mg strength has a white cap with the number “04” printed on it.
  - The capsule containing the 15 mg/16 mg strength has a yellow cap with the number “10” printed on it.
- Check to make sure you have received the prescribed strength of ENTRESTO SPRINKLE before taking or giving the dose.
Preparing to Take or Give ENTRESTO SPRINKLE
Supplies needed:
- A clean small bowl, cup, or spoon to measure and hold the soft food that you or your child likes, such as applesauce, yogurt, or pudding.
- Bottle with capsules containing ENTRESTO SPRINKLE.
Step 1. | Wash and dry your hands (Figure A). | Figure A
Step 2. | - Place the following items on a clean flat surface: - A small bowl, cup or spoon with about 1 to 2 teaspoonfuls of soft food that you or your child likes for each capsule of ENTRESTO SPRINKLE prescribed (see Figure B). - Bottle with capsules containing ENTRESTO SPRINKLE. - Check that you have the right strength of ENTRESTO SPRINKLE. | Figure B
Step 3. | Open the bottle and remove the number of capsules that you will need for your or your child’s prescribed dose of ENTRESTO SPRINKLE.
Step 4. | To open the capsule (see Figure C and Figure D):; - Hold the capsule upright (with the colored cap on top) so that the oral pellets are in the bottom of the capsule (Figure C). - Hold the capsule over the soft food. - Gently pinch the middle of the capsule and pull slightly to separate the 2 ends of the capsule (Figure D). Take care not to spill the contents while opening the capsule. | Figure C Figure D
Step 5. | Empty all of the oral pellets from the capsule onto the food (Figure E).; - Check the capsule to make sure that you did not miss any oral pellets. Tap the capsule to remove any remaining oral pellets. - Repeat Steps 4 and 5 if you need more than 1 capsule for the prescribed dose. | Figure E
Step 6. | Taking or Giving ENTRESTO SPRINKLE; - Take or give the food with the oral pellets right away after adding the oral pellets (Figure F). - Make sure that you or your child eat all of the food containing the oral pellets. - Make sure that you or your child do not chew the oral pellets to avoid a change of taste. | Figure F
Step 7. | Cleaning Up and Disposing of (throwing away) ENTRESTO SPRINKLE; - Throw away the empty shells of the capsule in the household trash (Figure G). - Wash your hands and all the items used to take or give ENTRESTO SPRINKLE.; Ask your pharmacist how to throw away expired medicines or medicines you no longer use. | Figure G
Storing ENTRESTO SPRINKLE
- Store ENTRESTO SPRINKLE at room temperature between 68°F to 77°F (20°C to 25°C).
- Protect ENTRESTO SPRINKLE from moisture.
Keep ENTRESTO SPRINKLE and all medicines out of the reach of children.
Distributed by: Novartis Pharmaceuticals Corporation East Hanover, New Jersey 07936
© Novartis
ENTRESTO is a registered trademark of Novartis AG
For more information, go to www.ENTRESTO.com or call 1-888-368-7378 (1-888-ENTRESTO).
This Instructions for Use has been approved by the U.S. Food and Drug Administration. |  | Issued: April 2024

T2024-30

PRINCIPAL DISPLAY PANEL

NDC 0078-0659-20

Entresto®

(sacubitril/valsartan) tablets

24 mg / 26 mg

Rx only

60 Tablets

NOVARTIS

PRINCIPAL DISPLAY PANEL

NDC 0078-0777-20

Entresto®

(sacubitril/valsartan) tablets

49 mg / 51 mg

Rx only

60 Tablets

NOVARTIS

PRINCIPAL DISPLAY PANEL

NDC 0078-0696-20

Entresto®

(sacubitril/valsartan) tablets

97 mg / 103 mg

Rx only

60 Tablets

NOVARTIS

PRINCIPAL DISPLAY PANEL

NDC 0078-1231-20

Entresto®
Sprinkle

(sacubitril/valsartan)
oral pellets

6 mg/6 mg

Open capsule shell to administer pellets.
Do Not swallow capsule whole.
Do Not chew or crush pellets.

Rx only

60 Capsules

NOVARTIS

PRINCIPAL DISPLAY PANEL

NDC 0078-1238-20

Entresto®
Sprinkle

(sacubitril/valsartan)
oral pellets

15 mg/16 mg

Open capsule shell to administer pellets.
Do Not swallow capsule whole.
Do Not chew or crush pellets.

Rx only

60 Capsules

NOVARTIS

PRINCIPAL DISPLAY PANEL

Physician Sample
Not for Sale

Entresto®

(sacubitril/valsartan) tablets

24 mg / 26 mg

Rx only

28 Tablets

NOVARTIS

PRINCIPAL DISPLAY PANEL

Physician Sample
Not for Sale

Entresto®

(sacubitril/valsartan) tablets

49 mg / 51 mg

Rx only

28 Tablets

NOVARTIS